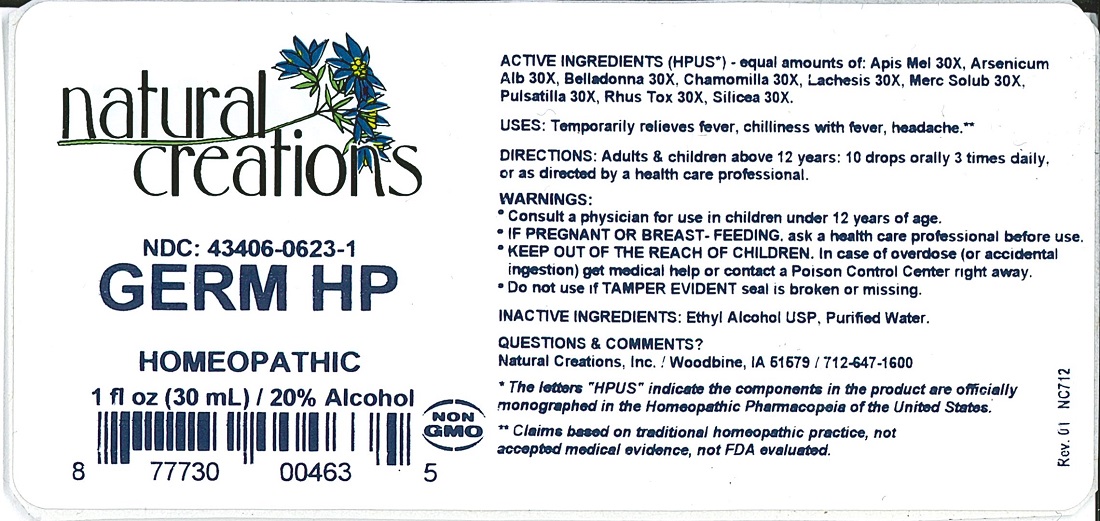 DRUG LABEL: GERM HP
NDC: 43406-0623 | Form: LIQUID
Manufacturer: Natural Creations, Inc.
Category: homeopathic | Type: HUMAN OTC DRUG LABEL
Date: 20251212

ACTIVE INGREDIENTS: APIS MELLIFERA 30 [hp_X]/1 mL; ARSENIC TRIOXIDE 30 [hp_X]/1 mL; ATROPA BELLADONNA 30 [hp_X]/1 mL; MATRICARIA RECUTITA 30 [hp_X]/1 mL; LACHESIS MUTA VENOM 30 [hp_X]/1 mL; MERCURIUS SOLUBILIS 30 [hp_X]/1 mL; PULSATILLA VULGARIS 30 [hp_X]/1 mL; TOXICODENDRON PUBESCENS LEAF 30 [hp_X]/1 mL; SILICON DIOXIDE 300 [hp_X]/1 mL
INACTIVE INGREDIENTS: ALCOHOL; WATER

GERM HP

ACTIVE INGREDIENT

Active Ingredients (HPUS*) - equal amounts of: Apis Mel 30X, Arsenicum Alb 30X, Belladonna 30X, Chamomilla 30X, Lachesis 30X, Merc Solub 30X, Pulsatilla 30X, Rhus Tox 30X, Silicea 30X.

PURPOSE

Uses: Temporarily relieves fever, chilliness with fever, headache.**

INDICATIONS AND USAGE

Uses: Temporarily relieves fever, chilliness with fever, headache.**

DOSAGE AND ADMINISTRATION

Directions: Adults & children above 12 years: 10 drops orally 3 times daily, or as directed by a health care professional.

KEEP OUT OF REACH OF CHILDREN

KEEP OUT OF THE REACH OF CHILDREN. In case of overdose (or accidental ingestion) get medical help or contact a Poison Control Center right away.

WARNINGS:

- Consult a physician for use in children under 12 years of age.
- IF PREGNANT OR BREAST-FEEDING, ask a health care professional before use.
- KEEP OUT OF THE REACH OF CHILDREN. In case of overdose (or accidental ingestion) get medical help or contact a Poison Control Center right away.
- Do not use if TAMPER EVIDENT seal is broken or missing.

Inactive Ingredients: Ethyl Alcohol USP, Purified Water.

Questions & Comments?

Natural Creations, Inc. / Woodbine, IA 51579 / 712-647-1600

REFERENCES

*The letters “HPUS” indicate the components in the product are officially monographed in the Homeopathic Pharmacopeia of the United States.

**Claims based on traditional homeopathic practice, not accepted medical evidence. Not FDA evaluated.

PACKAGE LABEL

NDC: 43406-0623-1

GERM HP

HOMEOPATHIC

1 fl oz (30 mL) 20% Alcohol

UPC: 877730004635 NON GMO Logo